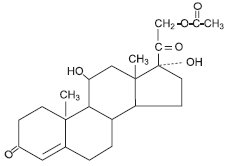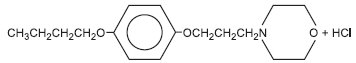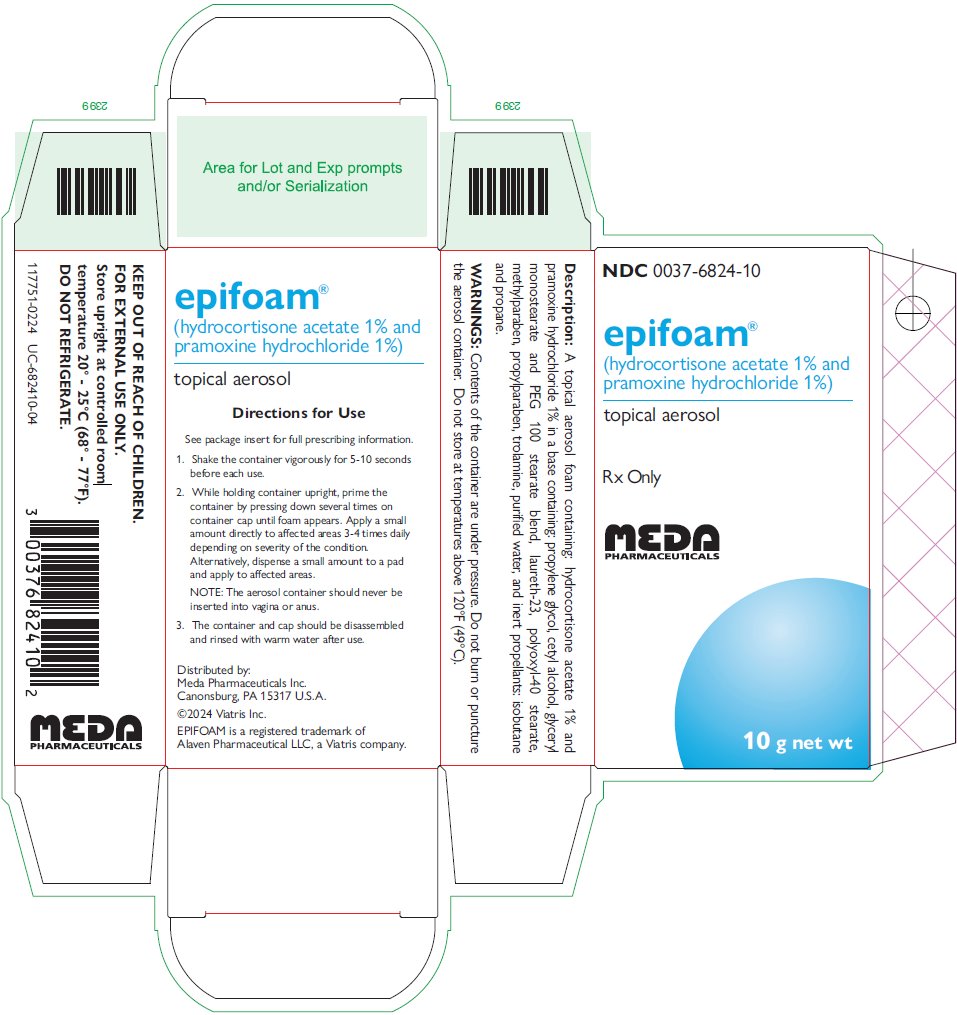 DRUG LABEL: EPIFOAM
NDC: 0037-6824 | Form: AEROSOL, FOAM
Manufacturer: Viatris Specialty LLC
Category: prescription | Type: HUMAN PRESCRIPTION DRUG LABEL
Date: 20240215

ACTIVE INGREDIENTS: PRAMOXINE HYDROCHLORIDE 100 mg/10 g; HYDROCORTISONE ACETATE 100 mg/10 g
INACTIVE INGREDIENTS: PROPYLENE GLYCOL; CETYL ALCOHOL; GLYCERYL MONOSTEARATE; PEG-100 STEARATE; LAURETH-23; POLYOXYL 40 STEARATE; METHYLPARABEN; PROPYLPARABEN; TROLAMINE; WATER; ISOBUTANE; PROPANE

DESCRIPTION

Epifoam® (hydrocortisone acetate 1% and pramoxine hydrochloride 1%) is a topical aerosol foam containing: hydrocortisone acetate 1% and pramoxine hydrochloride 1% in a base containing: propylene glycol, cetyl alcohol, glyceryl monostearate and PEG 100 stearate blend, laureth-23, polyoxyl-40 stearate, methylparaben, propylparaben, trolamine, purified water and inert propellants: isobutane and propane.

Epifoam® contains a synthetic corticosteroid used as an anti-inflammatory/antipruritic agent and a local anesthetic.

Hydrocortisone acetate

Molecular weight: 404.50. Solubility of hydrocortisone acetate in water: 1mg/100mL.

Chemical name: Pregn-4-ene-3, 20-dione, 21-(acetyloxy)-11, 17-dihydroxy-(11β)-.

Pramoxine hydrochloride

Molecular weight: 329.86. Pramoxine hydrochloride is freely soluble in water.

Chemical name: morpholine, 4-[3-(4- butoxyphenoxy) propyl]-, hydrochloride.

CLINICAL PHARMACOLOGY

Topical corticosteroids share anti-inflammatory, antipruritic and vasoconstrictive actions. The mechanism of anti-inflammatory activity of the topical corticosteroids is unclear. Various laboratory methods, including vasoconstrictor assays, are used to compare and predict potencies and/or clinical efficacies of the topical corticosteroids. There is some evidence to suggest that a recognizable correlation exists between vasoconstrictor potency and therapeutic efficacy in man.

Pramoxine Hydrochloride

A surface or local anesthetic which is not chemically related to the “caine” types of local anesthetics. Its unique chemical structure is likely to minimize the danger of cross-sensitivity reactions in patients allergic to other local anesthetics.

Pharmacokinetics

The extent of percutaneous absorption of topical corticosteroids is determined by many factors including the vehicle, the integrity of the epidermal barrier, and the use of occlusive dressings.

Topical corticosteroids can be absorbed from normal intact skin. Inflammation and/or disease processes in the skin increase the percutaneous absorption of topical corticosteroids. Occlusive dressings substantially increase the percutaneous absorption of topical corticosteroids. Thus, occlusive dressings may be a valuable therapeutic adjunct for treatment of resistant dermatoses. (See DOSAGE AND ADMINISTRATION.)

Once absorbed through the skin, topical corticosteroids are handled through pharmacokinetic pathways similar to systemically administered corticosteroids. Corticosteroids are bound to plasma proteins in varying degrees. Corticosteroids are metabolized primarily in the liver and are then excreted by the kidneys. Some of the topical corticosteroids and their metabolites are also excreted into the bile.

INDICATIONS AND USAGE

Topical corticosteroids are indicated for the relief of the inflammatory and pruritic manifestations of corticosteroid-responsive dermatoses.

CONTRAINDICATIONS

Topical corticosteroid products are contraindicated in those patients with a history of hypersensitivity to any of the components of the preparation.

WARNINGS

Not for prolonged use. If redness, pain, irritation or swelling persists, discontinue use and consult a physician. Contents of the container are under pressure. Do not burn or puncture the aerosol container. Do not store at temperatures above 120°F (49°C). Keep this and all medicines out of the reach of children.

PRECAUTIONS

General

Systemic absorption of topical corticosteroids has produced reversible hypothalamic-pituitary-adrenal (HPA) axis suppression, manifestations of Cushing’s syndrome, hyperglycemia and glucosuria in some patients.

Conditions which augment systemic absorption include the application of the more potent steroids, use over large surface areas, prolonged use and the addition of occlusive dressings.

Therefore, patients receiving a large dose of a potent topical steroid applied to a large surface area or under an occlusive dressing should be evaluated periodically for evidence of HPA axis suppression by using the urinary free cortisol and ACTH stimulation tests. If HPA axis suppression is noted, an attempt should be made to withdraw the drug, to reduce the frequency of application, or to substitute a less potent steroid.

Recovery of HPA axis function is generally prompt and complete upon discontinuation of the drug. Infrequently, signs and symptoms of steroid withdrawal may occur, requiring supplemental systemic corticosteroids.

In pediatric patients absorption may result in higher blood levels and thus more susceptibility to systemic toxicity. (See PRECAUTIONS-Pediatric Use.) If irritation develops, topical corticosteroids should be discontinued and appropriate therapy instituted.

In the presence of dermatological infections, the use of an appropriate antifungal or antibacterial agent should be instituted. If a favorable response does not occur promptly, the corticosteroid should be discontinued until the infection has been adequately controlled.

Information for the Patient

Patients using topical corticosteroids should receive the following information and instructions:

1. This medication is to be used as directed by the physician. It is for external use only. Avoid contact with the eyes.
2. Do not use this medication for any disorder other than for which it has been prescribed.
3. The treated skin area should not be bandaged or otherwise covered or wrapped as to be occlusive unless directed by the physician.
4. Report any signs of local adverse reactions especially under occlusive dressings.
5. Do not use any tight fitting diapers or plastic pants on a pediatric patient being treated in the diaper area, as these garments may constitute occlusive dressings.

Laboratory Tests

The following tests may be helpful in evaluating the HPA axis suppression:

Urinary free cortisol test
ACTH stimulation test

Carcinogenesis, Mutagenesis, and Impairment of Fertility

Long-term animal studies have not been performed to evaluate carcinogenic potential or the effect on fertility of topical corticosteroids.

Studies to determine mutagenicity with prednisolone and hydrocortisone have revealed negative results.

Pregnancy

Corticosteroids are generally teratogenic in laboratory animals when administered systemically at relatively low dosage levels. The more potent corticosteroids have been shown to be teratogenic after dermal application in laboratory animals. There are no adequate and well-controlled studies in pregnant women of teratogenic effects from topically applied corticosteroids. Therefore, topical corticosteroids should be used during pregnancy only if the potential benefit justifies the potential risk to the fetus. Drugs of this class should not be used extensively on pregnant patients, in large amounts, or for prolonged periods of time.

Nursing mothers

It is not known whether topical administration of corticosteroids could result in sufficient systemic absorption to produce detectable quantities in breast milk. Systemically administered corticosteroids are secreted into breast milk in quantities not likely to have a deleterious effect on the infant. Caution should be exercised when any topical corticosteroids are administered to a nursing woman.

Pediatric Use

PEDIATRIC PATIENTS MAY DEMONSTRATE GREATER SUSCEPTIBILTY TO TOPICAL CORTICOSTEROID-INDUCED HPA AXIS SUPPRESSION AND CUSHING’S SYNDROME THAN MATURE PATIENTS BECAUSE OF A LARGER SKIN SURFACE AREA TO BODY WEIGHT RATIO.

Hypothalamic-pituitary-adrenal (HPA) axis suppression, Cushing’s syndrome and intracranial hypertension have been reported in pediatric patients receiving topical corticosteroids. Manifestations of adrenal suppression in pediatric patients include linear growth retardation, delayed weight gain, low plasma cortisone levels and absence of response to ACTH stimulation. Manifestations of intracranial hypertension include bulging fontanelles, headaches, and bilateral papilledema.

Administration of topical corticosteroids to pediatric patients should be limited to the least amount compatible with an effective therapeutic regimen. Chronic corticosteroid therapy may interfere with the growth and development of pediatric patients.

Geriatric Use

Reported clinical experience has not identified differences in responses between the elderly and younger patients. In general, dose selection for an elderly patient should be cautious using the least amount compatible with an effective therapeutic regimen and reflecting the greater frequency of decreased hepatic, renal or cardiac function, and of concomitant disease or other drug therapy.

ADVERSE REACTIONS

To report SUSPECTED ADVERSE REACTIONS, contact Meda Pharmaceuticals Inc. at 1-877-848-6610 or FDA at 1-800-FDA-1088 or www.fda.gov/medwatch.

The following local adverse reactions are reported infrequently with topical corticosteroids, but may occur more frequently with the use of occlusive dressings. These reactions are listed in an approximately decreasing order of occurrence:

Burning, Itching, Irritation, Dryness, Folliculitis, Hypertrichosis, Acneiform eruptions, Hypopigmentation, Perioral dermatitis, Allergic contact dermatitis, Maceration of the skin, Secondary infection, Skin atrophy, Striae, Miliaria

OVERDOSAGE

Topically applied corticosteroids can be absorbed in sufficient amounts to produce systemic effects. (See PRECAUTIONS.)

DOSAGE AND ADMINISTRATION

Apply to affected area 3 to 4 times daily.

Occlusive dressings may be used for the management of psoriasis or recalcitrant conditions. If an infection develops, the use of occlusive dressings should be discontinued and appropriate antimicrobial therapy instituted.

Directions For Use:

1. Shake the container vigorously for 5-10 seconds before each use.
2. While holding container upright, prime the container by pressing down several times on container cap until foam appears. Apply a small amount directly to affected area 3-4 times daily depending on severity of the condition. Alternatively, dispense a small amount to a pad and apply to affected areas.
  NOTE: The aerosol container should never be inserted into vagina or anus.
3. The container and cap should be disassembled and rinsed with warm water after use.

HOW SUPPLIED

Epifoam® is supplied in 10 g pressurized cans.

NDC 0037-6824-10 10 g

Store upright at controlled room temperature 20° – 25°C (68° – 77°F).

DO NOT REFRIGERATE.

Distributed by:
Meda Pharmaceuticals Inc.
Canonsburg, PA 15317 U.S.A.

© 2024 Viatris Inc.

For Medical Inquiries,
call toll-free 1-877-848-6610

EPIFOAM is a registered trademark of Alaven Pharmaceutical LLC, a Viatris Company.

IN-682410-05

141341-0224

PRINCIPAL DISPLAY PANEL

NDC 0037-6824-10

epifoam®

(hydrocortisone acetate 1% and
pramoxine hydrochloride 1%)
topical aerosol

Rx Only

MEDA

10 g net wt

Description: A topical aerosol foam containing: hydrocortisone acetate 1% and
pramoxine hydrochloride 1% in a base containing: propylene glycol, cetyl alcohol, glyceryl
monostearate and PEG 100 stearate blend, laureth-23, polyoxyl-40 stearate,
methylparaben, propylparaben, trolamine, puried water, and inert propellants: isobutane
and propane.

WARNINGS: Contents of the container are under pressure. Do not burn or puncture
the aerosol container. Do not store at temperatures above 120°F (49°C).

Directions for Use

See package insert for full prescribing information.

1. Shake the container vigorously for 5-10 seconds
before each use.

2. While holding container upright, prime the
container by pressing down several times on
container cap until foam appears. Apply a small
amount directly to a‑ected areas 3-4 times daily
depending on severity of the condition.
Alternatively, dispense a small amount to a pad
and apply to a‑ected areas.

NOTE: The aerosol container should never be
inserted into vagina or anus.

3. The container and cap should be disassembled
and rinsed with warm water after use.

Distributed by:
Meda Pharmaceuticals Inc.
Canonsburg, PA 15317 U.S.A.

©2024 Viatris Inc.

EPIFOAM is a registered trademark of
Alaven Pharmaceutical LLC, a Viatris company.

KEEP OUT OF REACH OF CHILDREN.

FOR EXTERNAL USE ONLY.

Store upright at controlled room
temperature 20° - 25°C (68° - 77°F).

DO NOT REFRIGERATE.

117751-0224 UC-682410-04